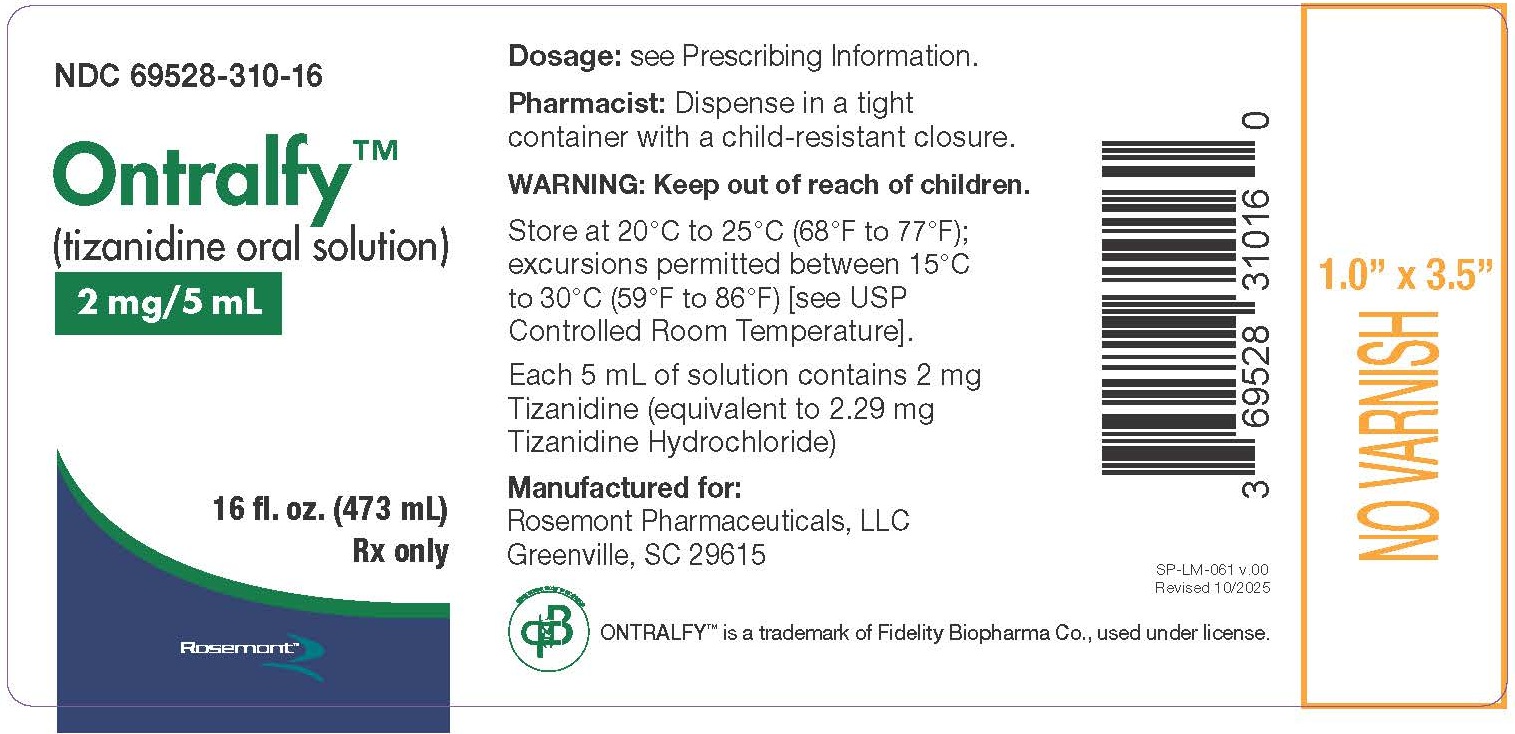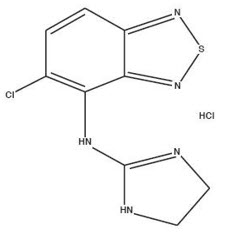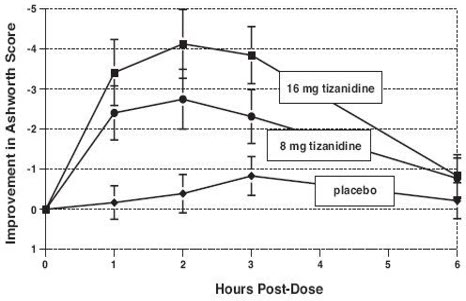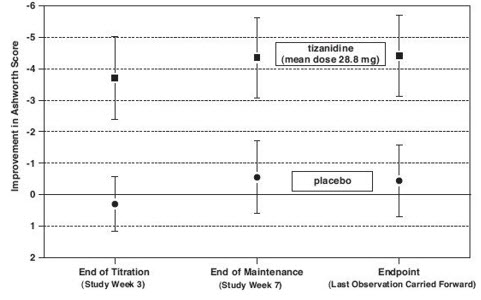 DRUG LABEL: Ontralfy
NDC: 69528-310 | Form: SOLUTION
Manufacturer: Rosemont Pharmaceuticals, LLC
Category: prescription | Type: HUMAN PRESCRIPTION DRUG LABEL
Date: 20251025

ACTIVE INGREDIENTS: TIZANIDINE HYDROCHLORIDE 2 mg/5 mL
INACTIVE INGREDIENTS: SUCRALOSE; METHYLPARABEN SODIUM; PROPYLPARABEN SODIUM; ANHYDROUS CITRIC ACID; ANHYDROUS TRISODIUM CITRATE; WATER; EDETATE DISODIUM

HIGHLIGHTS OF PRESCRIBING INFORMATION

These highlights do not include all the information needed to use ONTRALFY™ safely and effectively. See full prescribing information for ONTRALFY.
ONTRALFY™ (tizanidine oral solution)
Initial U.S. Approval: 1996

1 INDICATIONS AND USAGE

Ontralfy is a central alpha-2-adrenergic agonist indicated for the treatment of spasticity in adults. (1)

2 DOSAGE AND ADMINISTRATION

- Monitoring of aminotransferase levels is recommended at baseline and 1 month after maximum dose is achieved. (2.1)
- Recommended starting dose: 2 mg by mouth every 6 to 8 hours, as needed, up to a maximum of 3 doses in 24 hours. (2.2)
- Dosage can be increased by 2 mg to 4 mg per dose every 1 to 4 days; maximum total daily dosage is 36 mg. (2.2)
- The pharmacokinetics of Ontralfy differ when taken with or without food. These differences could result in a change in tolerability and control of symptoms. Consistent administration with respect to food is recommended. (2.2, 12.3)
- Patients with renal impairment (creatinine clearance <25 mL/min) or hepatic impairment: use lower individual doses during titration. If higher doses are required, individual doses rather than dosing frequency should be increased. (2.3, 2.4)
- To discontinue Ontralfy, decrease dose by 2 mg (5 mL) to 4 mg (10 mL) per day to minimize the risk of withdrawal adverse reactions. (2.5)

3 DOSAGE FORMS AND STRENGTHS

- Oral Solution: 2 mg/5 mL tizanidine (3)

4 CONTRAINDICATIONS

- Concomitant use with strong CYP1A2 inhibitors (4, 7.1)
- Patients with a history of hypersensitivity to tizanidine or the ingredients in Ontralfy (4, 5.5)

5 WARNINGS AND PRECAUTIONS

- Hypotension: monitor for signs and symptoms of hypotension, in particular in patients receiving concurrent antihypertensives; Ontralfy should not be used with other α2-adrenergic agonists. (5.1, 7.5)
- Risk of liver injury: monitor ALTs; discontinue Ontralfy if liver injury occurs. (5.2)
- Sedation: Ontralfy may interfere with everyday activities; sedative effects of Ontralfy, alcohol, and other central nervous system (CNS) depressants are additive. (5.3, 7.4)
- Hallucinations: consider discontinuation of Ontralfy. (5.4)

6 ADVERSE REACTIONS

The most common adverse reactions (greater than 10% of patients taking tizanidine and greater than in patients taking placebo) were dry mouth, somnolence, asthenia, and dizziness. (6.1)

To report SUSPECTED ADVERSE REACTIONS, contact Rosemont Pharmaceuticals, LLC at 1-844-638-2235 or FDA at 1-800-FDA-1088 or www.fda.gov/medwatch.

7 DRUG INTERACTIONS

Moderate or weak CYP1A2 inhibitors: avoid concomitant use; may cause hypotension, bradycardia, or excessive drowsiness; if concomitant use is necessary and adverse reactions occur, reduce Ontralfy dosage or discontinue. (7.2, 12.3)

8 USE IN SPECIFIC POPULATIONS

- Pregnancy: Based on animal data, may cause fetal harm. (8.1)
- Geriatric use: Ontralfy should be used with caution in elderly patients because clearance is decreased four-fold. (8.5)

FULL PRESCRIBING INFORMATION

1 INDICATIONS AND USAGE

Ontralfy is indicated for the treatment of spasticity in adults.

2 DOSAGE AND ADMINISTRATION

2.1 Recommended Evaluation and Testing Before and After Initiating Ontralfy

Monitoring of aminotransferase levels is recommended at baseline and 1 month after maximum dose is achieved [see Warnings and Precautions (5.2)].

2.2 Recommended Dosage

The recommended starting dose is 2 mg (5 mL) by mouth every 6 to 8 hours, as needed, to a maximum of three doses in 24 hours.

Dosage can be gradually increased every 1 to 4 days by 2 mg (5 mL) to 4 mg (10 mL) at each dose based on clinical response and tolerability. The maximum total daily dosage is 36 mg (90 mL). Single doses greater than 16 mg (40 mL) have not been studied.

The pharmacokinetics of Ontralfy differ when taken with or without food [see Clinical Pharmacology (12.3)]. Ontralfy may be taken with or without food; however, consistent administration with respect to food is recommended to reduce variability in tizanidine plasma exposure .If administration with respect to food is changed, monitor patients for therapeutic effect or adverse reactions [see Clinical Pharmacology (12.3)].

Because of the short duration of therapeutic effect, treatment with Ontralfy should be reserved for those daily activities and times when relief of spasticity is most important.

2.3 Recommended Dosage in Patients with Renal Impairment

In patients with creatinine clearance < 25 mL/min, use lower individual doses during titration. If higher doses are required, the individual doses rather than dosing frequency should be increased [see Use in Specific Populations (8.6)and Clinical Pharmacology (12.3)].

2.4 Recommended Dosage in Patients with Hepatic Impairment

In patients with hepatic impairment, use lower individual doses during titration. If higher doses are required, individual doses rather than dosing frequency should be increased [see Use in Specific Populations (8.7)and Clinical Pharmacology (12.3)].

2.5 Discontinuation of Ontralfy

When discontinuing Ontralfy, particularly in patients who have been receiving high doses for long periods or who may be on concomitant treatment with narcotics, decrease the dosage by 2 mg (5 mL) to 4 mg (10 mL) per day to minimize the risk of withdrawal adverse reactions [see Drug Abuse and Dependence (9.3)].

3 DOSAGE FORMS AND STRENGTHS

Oral Solution: 2 mg/5 mL of tizanidine as a clear, colorless to pale yellow solution with a strawberry flavor.

4 CONTRAINDICATIONS

Ontralfy is contraindicated in patients:

- taking strong CYP1A2 inhibitors [see Drug Interactions (7.1)].
- with a history of hypersensitivity to tizanidine or the ingredients in Ontralfy. Symptoms have included anaphylaxis and angioedema [see Warnings and Precautions (5.5)]

5 WARNINGS AND PRECAUTIONS

5.1 Hypotension

Ontralfy is an α2-adrenergic agonist that can produce hypotension [see Adverse Reactions (6.1)and Drug Interactions (7.5)] . Syncope has been reported in patients treated with tizanidine in the postmarketing setting. The risk of hypotension may be minimized by dose titration; monitoring for signs and symptoms of hypotension prior to dosage increase may minimize the risks associated with hypotension. In addition, patients moving from a supine to fixed upright position may be at increased risk for hypotension and orthostatic effects.

Monitor for hypotension when Ontralfy is used in patients receiving concurrent antihypertensive therapy. It is not recommended that Ontralfy be used with other α2-adrenergic agonists. Clinically significant hypotension (decreases in both systolic and diastolic pressure) has been reported with concomitant administration of tizanidine and strong CYP1A2 inhibitors [see Clinical Pharmacology (12.3)] . Therefore, concomitant use of Ontralfy with strong CYP1A2 inhibitors is contraindicated [see Contraindications (4)and Drug Interactions (7.1)] .

5.2 Liver Injury

Ontralfy may cause hepatocellular liver injury. Liver function test abnormality and hepatotoxicity have been observed with tizanidine, the active moiety of Ontralfy [see Adverse Reactions (6.1, 6.2)]. Monitoring of aminotransferase levels is recommended at baseline and 1 month after maximum dose is achieved, or if hepatic injury is suspected [see Dosage and Administration (2.1)and Use in Specific Populations (8.7)].

5.3 Sedation

Ontralfy can cause sedation, which may interfere with everyday activity. In the multiple dose studies of tizanidine, the prevalence of patients with sedation peaked following the first week of titration and then remained stable for the duration of the maintenance phase of the study [see Adverse Reactions (6.1)] . The CNS depressant effects of Ontralfy with alcohol and other CNS depressants (e.g., benzodiazepines, opioids, tricyclic antidepressants) may be additive [see Drug Interactions (7.4)] . Monitor patients who take Ontralfy with another CNS depressant for symptoms of excess sedation .

5.4 Hallucinosis/Psychotic-Like Symptoms

Tizanidine use has been associated with hallucinations. Formed, visual hallucinations or delusions were reported in 5 of 170 patients (3%) in two North American controlled clinical studies of tizanidine. Most of the patients were aware that the events were unreal. One patient developed psychosis in association with the hallucinations. One patient among these 5 continued to have problems for at least 2 weeks following discontinuation of tizanidine. Hallucinations have also been reported with tizanidine use in the postmarketing setting. Consider discontinuing Ontralfy in patients who develop hallucinations.

5.5 Hypersensitivity Reactions

Ontralfy can cause anaphylaxis. Signs and symptoms of hypersensitivity, including respiratory compromise, urticaria, and angioedema of the throat and tongue, have been reported. Ontralfy is contraindicated in patients with a history of hypersensitivity reactions to tizanidine [see Contraindications (4)].

5.6 Withdrawal Adverse Reactions

Ontralfy can cause withdrawal adverse reactions, which include rebound hypertension, tachycardia, and hypertonia. To minimize the risk of these reactions, particularly in patients who have been receiving high doses of Ontralfy (20 to 28 mg daily) for long periods of time (9 weeks or more) or who may be on concomitant treatment with narcotics, the Ontralfy dosage should be decreased slowly [see Dosage and Administration (2.5)].

6 ADVERSE REACTIONS

The following clinically significant adverse reactions are described elsewhere in other sections of the prescribing information:

- Hypotension [see Warnings and Precautions (5.1)]
- Liver Injury [see Warnings and Precautions (5.2)]
- Sedation [see Warnings and Precautions (5.3)]
- Hallucinosis/Psychotic-Like Symptoms [see Warnings and Precautions (5.4)]
- Hypersensitivity Reactions [see Warnings and Precautions (5.5)]
- Withdrawal Adverse Reactions [see Warnings and Precautions (5.6)]

6.1 Clinical Trials Experience

Because clinical studies are conducted under widely varying conditions, adverse reaction rates observed in the clinical studies of a drug cannot be directly compared to rates in the clinical studies of another drug and may not reflect the rates observed in practice.

The safety of Ontralfy has been established from adequate and well-controlled studies of tizanidine tablets in adult patients with spasticity [see Clinical Studies (14)] . Below is a presentation of the adverse reactions of tizanidine tablets in these adequate and well-controlled studies.

The safety of tizanidine has been evaluated in three double-blind, randomized, placebo-controlled clinical studies [see Clinical Studies (14)] . Two studies were conducted in patients with multiple sclerosis and one in patients with spinal cord injury. Each study had a 13-week active treatment period which included a 3-week titration phase to the maximum tolerated dose up to 36 mg/day in three divided doses, a 9-week plateau phase where the dose of tizanidine was held constant and a 1-week dose tapering period. In all, 264 patients received tizanidine and 261 patients received placebo. Across the three studies approximately 51% of patients were women, and the median dose during the plateau phase ranged from 20 to 28 mg/day.

The most common adverse reactions (>10% of patients treated with tizanidine) reported in multiple dose, placebo-controlled clinical studies involving 264 patients with spasticity were dry mouth, somnolence/sedation, asthenia (weakness, fatigue and/or tiredness), and dizziness. Three-quarters of the patients rated the reactions as mild to moderate and one-quarter of the patients rated the reactions as being severe. These adverse reactions appeared to be dose related.

Table 1 lists adverse reactions that were reported in greater than 2% of patients in three multiple dose, placebo-controlled studies who received tizanidine where the frequency in the tizanidine group was greater than the placebo group.

Table 1: Multiple Dose, Placebo-Controlled Studies Adverse Reactions Reported in >2% of Patients Treated with Tizanidine Tablets and Incidence Greater than Placebo

Adverse Reaction | Placebo; N = 261; % | Tizanidine Tablet N = 264; %
Dry mouth | 10 | 49
Somnolence | 10 | 48
Asthenia* | 16 | 41
Dizziness | 4 | 16
UTI | 7 | 10
Infection | 5 | 6
Liver test abnormality | 2 | 6
Constipation | 1 | 4
Vomiting | 0 | 3
Speech disorder | 0 | 3
Amblyopia (blurred vision) | <1 | 3
Urinary frequency | 2 | 3
Flu syndrome | 2 | 3
Dyskinesia | 0 | 3
Nervousness | <1 | 3
Pharyngitis | 1 | 3
Rhinitis | 2 | 3

* includes weakness, fatigue, and/or tiredness

In the single dose, placebo-controlled study involving 142 patients with spasticity due to multiple sclerosis (Study 1) [see Clinical Studies (14)] , the patients were specifically asked if they had experienced any of the four most common adverse reactions: dry mouth, somnolence (drowsiness), asthenia (weakness, fatigue and/or tiredness), and dizziness. In addition, hypotension and bradycardia were observed. The occurrence of these reactions is summarized in Table 2. Other events were, in general, reported at a rate of 2% or less.

Table 2: Single Dose, Placebo-Controlled Study—Common Adverse Reactions Reported

Adverse Reaction | Placebo; N = 48; % | Tizanidine; Tablet,; 8 mg, N = 45; % | Tizanidine Tablet,; 16 mg,; N = 49; %
Somnolence | 31 | 78 | 92
Dry mouth | 35 | 76 | 88
Asthenia* | 40 | 67 | 78
Dizziness | 4 | 22 | 45
Hypotension | 0 | 16 | 33
Bradycardia | 0 | 2 | 10

* includes weakness, fatigue, and/or tiredness

6.2 Postmarketing Experience

The following adverse reactions have been identified during post approval use of tizanidine. Because these reactions are reported voluntarily from a population of uncertain size, it is not always possible to reliably estimate their frequency or establish a causal relationship to drug exposure.

Cardiac Disorders: Ventricular tachycardia, decreased blood pressure

Hepatobiliary Disorders: Hepatotoxicity [see Warnings and Precautions (5.2)] , hepatitis

Musculoskeletal and Connective Tissue Disorders: arthralgia

Nervous System Disorders: Convulsion, paresthesia, tremor, muscle spasms

Psychiatric Disorders: Hallucinations [see Warnings and Precautions (5.4)], depression

Skin and Subcutaneous Tissue Disorders: Stevens Johnson Syndrome, anaphylactic reaction [see Warnings and Precautions (5.5)] , exfoliative dermatitis, rash

7 DRUG INTERACTIONS

7.1 Strong CYP1A2 Inhibitors

Concomitant use of Ontralfy with strong cytochrome P450 1A2 (CYP1A2) inhibitors (e.g., fluvoxamine, ciprofloxacin) is contraindicated. Changes in pharmacokinetics of tizanidine when administered with a strong CYP1A2 inhibitor resulted in significantly decreased blood pressure, increased drowsiness, and increased psychomotor impairment [see Contraindications (4)and Clinical Pharmacology (12.3)].

7.2 Moderate or Weak CYP1A2 Inhibitors

Concomitant use of Ontralfy with moderate or weak CYP1A2 inhibitors (e.g., zileuton, antiarrhythmics [amiodarone, mexiletine, propafenone, and verapamil], cimetidine, famotidine, oral contraceptives, acyclovir, and ticlopidine) should be avoided. If concomitant use is clinically necessary, and adverse reactions such as hypotension, bradycardia, or excessive drowsiness occur, reduce Ontralfy dosage or discontinue Ontralfy therapy [see Clinical Pharmacology (12.3)].

7.3 Oral Contraceptives

Concomitant use of Ontralfy with oral contraceptives is not recommended. However, if concomitant use is clinically necessary and adverse reactions such as hypotension, bradycardia, or excessive drowsiness occur, reduce or discontinue Ontralfy therapy [see Clinical Pharmacology (12.3)].

7.4 Alcohol and Other CNS Depressants

Alcohol increases the exposure of tizanidine after administration of Ontralfy. This was associated with an increase in adverse reactions of tizanidine.

Concomitant use of Ontralfy with CNS depressants (e.g., alcohol, benzodiazepines, opioids, tricyclic antidepressants) may cause additive CNS depressant effects, including sedation. Monitor patients who take Ontralfy with another CNS depressant for symptoms of excess sedation [see Clinical Pharmacology (12.3)].

7.5 α2-Adrenergic Agonists

Concomitant use of Ontralfy with other α2-adrenergic agonists is not recommended because hypotensive effects may be cumulative [see Warnings and Precautions (5.1)].

7.6 Antihypertensive Medications

Concomitant use of Ontralfy with antihypertensive medications may cause additive hypotensive effects [see Warnings and Precautions (5.1)] . Monitor patients who take Ontralfy with antihypertensive medications for hypotension.

8 USE IN SPECIFIC POPULATIONS

8.1 Pregnancy

Risk Summary

There are no adequate data on the developmental risk associated with use of tizanidine in pregnant women. In animal studies, administration of tizanidine during pregnancy resulted in developmental toxicity (embryofetal and postnatal offspring mortality and growth deficits) at doses less than those used clinically, which were not associated with maternal toxicity (see Animal Data).

In the U.S. general population, the estimated background risk of major birth defects and miscarriage in clinically recognized pregnancies is 2% - 4% and 15% - 20%, respectively. The background risk of major birth defects and miscarriage for the indicated population is unknown.

Data

Animal Data

Oral administration of tizanidine (0.3 to 100 mg/kg/day) to pregnant rats during the period of organogenesis resulted in embryofetal and postnatal offspring mortality and reductions in body weight at doses of 30 mg/kg/day and above. Maternal toxicity was observed at the highest dose tested. The no-effect dose for embryofetal developmental toxicity in rats (3 mg/kg/day) is similar to the maximum recommended human dose (MRHD) of 36 mg/day on a body surface area (mg/m^2) basis.

Oral administration of tizanidine (1 to 100 mg/kg/day) to pregnant rabbits during the period of organogenesis resulted in embryofetal and postnatal offspring mortality at all doses. Maternal toxicity was observed at the highest dose tested. Oral administration of tizanidine (10 and 30 mg/kg/day) during the perinatal period of pregnancy (2-6 days prior to delivery) resulted in increased postnatal offspring mortality at both doses. A no-effect dose for embryofetal developmental toxicity in rabbit was not identified. The lowest dose tested (1 mg/kg/day) is less than the MRHD on a mg/m^2basis.

In a pre- and postnatal development study in rats, oral administration of tizanidine (3 to 30 mg/kg/day) resulted in increased postnatal offspring mortality. A no-effect dose for pre- and postnatal developmental toxicity was not identified. The lowest dose tested (3 mg/kg/day) is similar to the MRHD on a mg/m^2basis, respectively.

8.2 Lactation

Risk Summary

There are no data on the presence of tizanidine in human milk, the effects on the breastfed infant, or the effects on human milk production. Animal studies have reported the presence of tizanidine in the milk of lactating animals.

The developmental and health benefits of breastfeeding should be considered along with the mother's clinical need for Ontralfy and any potential adverse effects on the breastfed infant from Ontralfy or from the underlying maternal condition.

8.3 Females and Males of Reproductive Potential

There are no adequate and well-controlled studies in humans on the effect of Ontralfy on female or male reproductive potential. Oral administration of tizanidine to male and female rats resulted in adverse effects on fertility [see Nonclinical Toxicology (13.1)].

8.4 Pediatric Use

Safety and effectiveness in pediatric patients have not been established.

Juvenile Animal Toxicity Data

Oral administration of tizanidine (0, 1, 3, and 10 mg/kg/day) to juvenile rats from postnatal day (PND) 7 through PND 70 resulted in delayed sexual maturation in males at all doses, reduced body weight gain, delayed sexual maturation in females, and bilateral corneal crystals at the mid and high doses. Corneal crystals were still observed at the mid and high doses after a three-week recovery period. Neurobehavioral deficits were observed on a learning and memory task at the high dose. A no-effect dose for adverse effects on postnatal development was not identified.

8.5 Geriatric Use

Tizanidine is known to be substantially excreted by the kidney, and the risk of adverse reactions to this drug may be greater in patients with impaired renal function. Because elderly patients are more likely to have decreased renal function, care should be taken in dose selection, and it may be useful to monitor renal function.

Clinical studies of tizanidine did not include sufficient numbers of subjects aged 65 and over to determine whether they respond differently than younger subjects. Pharmacokinetic data showed that elderly subjects cleared tizanidine slower than the younger subjects [see Clinical Pharmacology (12.3)] . In elderly patients with renal insufficiency (creatinine clearance < 25 mL/min), tizanidine clearance is reduced compared to healthy elderly subjects; this would be expected to lead to a longer duration of clinical effect. During titration, the individual doses should be reduced. If higher doses are required, individual doses rather than dosing frequency should be increased. Monitor elderly patients because they may have an increased risk for adverse reactions associated with Ontralfy.

8.6 Renal Impairment

In patients with renal insufficiency (creatinine clearance < 25 mL/min), clearance of tizanidine was reduced [see Clinical Pharmacology (12.3)] . In these patients, dosage reduction is recommended [see Dosage and Administration (2.3)] . Because the risk of adverse reactions to Ontralfy may be greater in patients with impaired renal function, monitor these patients closely for the onset or increase in severity of common adverse reactions [see Adverse Reactions (6.1)] .

8.7 Hepatic Impairment

Ontralfy should be used with caution in patients with hepatic impairment. The influence of hepatic impairment on the pharmacokinetics of tizanidine has not been evaluated. Because tizanidine is extensively metabolized in the liver, hepatic impairment would be expected to have significant effects on pharmacokinetics of tizanidine [see Warnings and Precautions (5.2), and Clinical Pharmacology (12.3)]. In patients with hepatic impairment, dosage reduction is recommended [see Dosage and Administration (2.4)].

9 DRUG ABUSE AND DEPENDENCE

9.1 Controlled Substance

Ontralfy contains tizanidine, which is not a controlled substance.

9.2 Abuse

Abuse is the intentional, non-therapeutic use of a drug, even once, for its desirable psychological or physiological effects. Abuse potential was not evaluated in human studies. Rats were able to distinguish tizanidine from saline in a standard discrimination paradigm, after training, but failed to generalize the effects of morphine, cocaine, diazepam, or phenobarbital to tizanidine.

9.3 Dependence

Physical dependence is a state that develops as a result of physiological adaptation in response to repeated drug use, manifested by withdrawal signs and symptoms after abrupt discontinuation or a significant dose reduction of a drug. Tizanidine is closely related to clonidine, which is often abused in combination with narcotics and is known to cause symptoms of rebound upon abrupt withdrawal. Cases of rebound symptoms on sudden withdrawal of tizanidine have been reported. The case reports suggest that these patients were also misusing narcotics. Withdrawal symptoms included hypertension, tachycardia, hypertonia, tremor, and anxiety. Withdrawal symptoms are more likely to occur in cases where high doses are used, especially for prolonged periods, or with concomitant use of narcotics. If therapy needs to be discontinued, the dose should be decreased slowly to minimize the risk of withdrawal symptoms [see Dosage and Administration (2.5)].

Monkeys were shown to self-administer tizanidine in a dose-dependent manner, and abrupt cessation of tizanidine produced transient signs of withdrawal at doses > 35 times the maximum recommended human dose on a mg/m^2basis. These transient withdrawal signs (increased locomotion, body twitching, and aversive behavior toward the observer) were not reversed by naloxone administration.

10 OVERDOSAGE

A review of the safety surveillance database revealed cases of intentional and accidental tizanidine overdose. Some of the cases resulted in fatality and many of the intentional overdoses were with multiple drugs including CNS depressants. The clinical manifestations of tizanidine overdose were consistent with its known pharmacology. In the majority of cases a decrease in sensorium was observed including lethargy, somnolence, confusion and coma. Depressed cardiac function is also observed including most often bradycardia and hypotension. Respiratory depression is another common feature of tizanidine overdose.

Should overdose occur, ensure the adequacy of an airway and monitor cardiovascular and respiratory function. Dialysis is not likely to be an efficient method of removing tizanidine from the body [see Description (11)]. In general, symptoms resolve within one to three days following discontinuation of tizanidine and administration of appropriate therapy. Because of the similar mechanism of action, symptoms and management of tizanidine overdose are similar to that following clonidine overdose. For the most recent information concerning the management of overdose, contact a poison control center.

11 DESCRIPTION

Ontralfy contains tizanidine hydrochloride as the active ingredient, which is a central alpha2-adrenergic agonist. Its chemical name is 5-chloro-4-(2-imidazolin-2-ylamino)-2,1,3-benzothiadiazole monohydrochloride. It has a molecular formula of C9H8ClN5S.HCl and a molecular weight of 290.2. Its structural formula is:

Tizanidine hydrochloride is a white to off-white, fine crystalline powder, which is odorless or with a faint characteristic odor. Tizanidine hydrochloride is slightly soluble in water and methanol; solubility in water decreases as the pH increases.

Ontralfy is supplied as an oral solution. Each 5 mL contains 2 mg tizanidine (equivalent to 2.29 mg tizanidine hydrochloride), and the inactive ingredients anhydrous citric acid, edetate disodium dihydrate, flavor, methylparaben sodium, propylparaben sodium, purified water, sodium citrate anhydrous, and sucralose. Each 5 mL of Ontralfy contains 2 mg of sodium.

12 CLINICAL PHARMACOLOGY

12.1 Mechanism of Action

Tizanidine is a central alpha-2-adrenergic receptor agonist and presumably reduces spasticity by increasing presynaptic inhibition of motor neurons. The effects of tizanidine are greatest on polysynaptic pathways. The overall effect of these actions is thought to reduce facilitation of spinal motor neurons.

12.2 Pharmacodynamics

The CNS depressant effects of tizanidine and alcohol are additive [see Warnings and Precautions (5.3)and Drug Interactions (7.4)] .

12.3 Pharmacokinetics

Tizanidine has linear pharmacokinetics over the doses studied in clinical development [1 mg (half the recommended dosage) to 20 mg]. Ontralfy oral solution has comparable bioavailability to tizanidine oral tablets under fasted and fed conditions and to tizanidine oral capsules under the fed condition.

Absorption

Following oral administration, tizanidine is essentially completely absorbed. The absolute oral bioavailability of tizanidine is approximately 40% (CV = 24%), due to extensive first-pass hepatic metabolism.

Effect of Food

In a single dose pharmacokinetic study in healthy adult subjects, the administration of Ontralfy following a standardized high-fat, high-calorie breakfast had minimal effect on the Cmaxof tizanidine; however, AUC was increased by approximately 33% when compared to dosing under fasting condition. The median Tmaxand mean elimination half-life (t1/2) are similar under both fasting and fed conditions.

Distribution

Tizanidine is extensively distributed throughout the body with a mean steady state volume of distribution of 2.4 L/kg (CV = 21%) following intravenous administration in healthy adult volunteers. Tizanidine is approximately 30% bound to plasma proteins.

Elimination

Metabolism

Tizanidine has a half-life of approximately 2.5 hours (CV=33%). Approximately 95% of an administered dose is metabolized. The primary cytochrome P450 isoenzyme involved in tizanidine metabolism is CYP1A2. Tizanidine metabolites are not known to be active; their half- lives range from 20 to 40 hours.

Excretion

Following single and multiple oral dosing of^14C-tizanidine, an average of 60% and 20% of total radioactivity was recovered in the urine and feces, respectively.

Specific Populations

Geriatric Patients

No specific pharmacokinetic study was conducted to investigate age effects. Cross study comparison of pharmacokinetic data following single dose administration of 6 mg tizanidine showed that elderly subjects cleared the drug four times slower than younger subjects [see Use in Specific Populations (8.5)].

Patients with Hepatic Impairment

The influence of hepatic impairment on the pharmacokinetics of tizanidine has not been evaluated. Because tizanidine is extensively metabolized in the liver, hepatic impairment would be expected to have significant effects on pharmacokinetics of tizanidine [see Use in Specific Populations (8.7)].

Patients with Renal Impairment

Tizanidine clearance is reduced by more than 50% in elderly patients with renal insufficiency (creatinine clearance < 25 mL/min) compared to healthy elderly subjects; this would be expected to lead to a longer duration of clinical effect. [see Use in Specific Populations (8.6)].

Gender Effects

No specific pharmacokinetic study was conducted to investigate gender effects. Retrospective analysis of pharmacokinetic data following single and multiple dose administration of 4 mg tizanidine, however, showed that gender had no effect on the pharmacokinetics of tizanidine.

Drug Interactions

CYP1A2 Inhibitors

The effects of coadministration of fluvoxamine or ciprofloxacin, both strong CYP1A2 inhibitors, on the pharmacokinetics of a single 4 mg dose of tizanidine was studied in 10 healthy subjects. The Cmax, AUC, and half-life of tizanidine increased by 12-fold, 33-fold, and 3-fold, respectively, with coadministration of fluvoxamine. The Cmaxand AUC of tizanidine increased by 7-fold and 10-fold, respectively, with coadministration of ciprofloxacin [see Contraindications (4)].

There have been no clinical studies evaluating the effects of other CYP1A2 inhibitors on tizanidine [see Drug Interactions (7.2)] .

In vitro studies of cytochrome P450 isoenzymes using human liver microsomes indicate that neither tizanidine nor the major metabolites are likely to affect the metabolism of other drugs metabolized by cytochrome P450 isoenzymes.

Oral Contraceptives

No specific pharmacokinetic study was conducted to investigate interaction between oral contraceptives and Ontralfy. Retrospective analysis of population pharmacokinetic data following single and multiple dose administration of 4 mg tizanidine, however, showed that women concurrently taking oral contraceptives had 50% lower clearance of tizanidine compared to women not on oral contraceptives [see Drug Interactions (7.3)].

Acetaminophen

Tizanidine delayed the Tmaxof acetaminophen by 16 minutes. Acetaminophen did not affect the pharmacokinetics of tizanidine.

Alcohol

Alcohol increased the AUC and Cmaxof tizanidine by approximately 20% and 15%, respectively [see Drug Interactions (7.4)].

13 NONCLINICAL TOXICOLOGY

13.1 Carcinogenesis, Mutagenesis, Impairment of Fertility

Carcinogenesis

Tizanidine was administered to mice for 78 weeks at oral doses up to 16 mg/kg/day, which is 2 times the maximum recommended human dose (MRHD) of 36 mg/day on a body surface area (mg/m^2) basis. Tizanidine was administered to rats for 104 weeks at oral doses up to 9 mg/kg/day, which is 2.5 times the MRHD on a mg/m^2basis. There was no increase in tumors in either species.

Mutagenesis

Tizanidine was negative in in vitro(bacterial reverse mutation [Ames], mammalian gene mutation, and chromosomal aberration test in mammalian cells) and in vivo(bone marrow micronucleus, and cytogenetics) assay.

Impairment of Fertility

Oral administration of tizanidine to rats prior to and during mating and continuing during early pregnancy in females resulted in reduced fertility in male and female rats at doses of 30 and 10 mg/kg/day, respectively. No effect on fertility was observed at doses of 10 (male) and 3 (female) mg/kg/day, which are approximately 3 times and similar to the MRHD, respectively, on a mg/m^2basis.

14 CLINICAL STUDIES

The efficacy of Ontralfy is supported by evidence from a relative bioavailability study in healthy adult subjects comparing Ontralfy to tizanidine tablets under fasted and fed conditions [see Clinical Pharmacology (12.3)]. The clinical studies described below were conducted using tizanidine tablets.

The efficacy of tizanidine for the treatment of spasticity was demonstrated in two adequate and well-controlled studies in patients with multiple sclerosis or spinal cord injury (Studies 1 and 2).

Single-Dose Study in Patients with Multiple Sclerosis with Spasticity

In Study 1, 140 patients with spasticity caused by multiple sclerosis were randomized to receive single oral doses of 8 mg or 16 mg tizanidine, or placebo. Patients and assessors were blinded to treatment assignment and efforts were made to reduce the likelihood that assessors would become aware indirectly of treatment assignment (e.g., they did not provide direct care to patients and were prohibited from asking questions about side effects).

Response was assessed by physical examination; muscle tone was rated on a 5-point scale (Ashworth score) as follows:

- 0 = normal muscle tone
- 1 = slight spastic catch
- 2 = more marked muscle resistance
- 3 = considerable increase in tone, making passive movement difficult
- 4 = a muscle immobilized by spasticity

Spasm counts were also collected.

Assessments were made at 1, 2, 3 and 6 hours after treatment. A statistically significant reduction of the Ashworth score for tizanidine compared to placebo was detected at 1, 2 and 3 hours after treatment. Figure 1 below shows a comparison of the mean change in muscle tone from baseline as measured by the Ashworth scale. The greatest reduction in muscle tone was 1 to 2 hours after treatment. By 6 hours after treatment, muscle tone in the 8 mg and 16 mg tizanidine groups was indistinguishable from muscle tone in patients who received placebo. Within a given patient, improvement in muscle tone was correlated with plasma concentration. Plasma concentrations were variable from patient to patient at a given dose. Although 16 mg produced a larger effect, adverse reactions including hypotension were more common and more severe than in the 8 mg group. There were no differences in the number of spasms occurring in each group.

Figure 1: Single Dose Study—Mean Change in Muscle Tone from Baseline as Measured by the Ashworth Scale ± 95% Confidence Interval (A Negative Ashworth Score Signifies an Improvement in Muscle Tone from Baseline)

Seven-Week Study in Patients with Spinal Cord Injury with Spasticity

In a 7-week study (Study 2), 118 patients with spasticity secondary to spinal cord injury were randomized to either placebo or tizanidine. Steps similar to those taken in the first study were employed to ensure the integrity of blinding.

Patients were titrated over 3 weeks up to a maximum tolerated dose or 36 mg daily given in three unequal doses (e.g., 10 mg given in the morning and afternoon and 16 mg given at night). Patients were then maintained on their maximally tolerated dose for 4 additional weeks (i.e., maintenance phase). Throughout the maintenance phase, muscle tone was assessed on the Ashworth scale within a period of 2.5 hours following either the morning or afternoon dose. The number of daytime spasms was recorded daily by patients.

At endpoint (the protocol-specified time of outcome assessment), there was a statistically significant reduction in muscle tone and frequency of spasms in the tizanidine treated group compared to placebo. The reduction in muscle tone was not associated with a reduction in muscle strength (a desirable outcome) but also did not lead to any consistent advantage of tizanidine treated patients on measures of activities of daily living. Figure 2 below shows a comparison of the mean change in muscle tone from baseline as measured by the Ashworth scale.

Figure 2: Seven Week Study—Mean Change in Muscle Tone 0.5–2.5 Hours After Dosing as Measured by the Ashworth Scale ± 95% Confidence Interval (A Negative Ashworth Score Signifies an Improvement in Muscle Tone from Baseline)

16 HOW SUPPLIED/STORAGE AND HANDLING

16.1 How Supplied

Ontralfy contains 2 mg/5 mL tizanidine. It is a clear, colorless to pale yellow solution with strawberry flavor and is supplied in bottles of 473 mL with child-resistant closure (NDC 69528-310-16).

16.2 Storage and Handling

Store at 20°C to 25°C (68°F to 77°F); excursions permitted between 15°C to 30°C (59°F to 86°F) [see USP Controlled Room Temperature].

Dispense in containers with child-resistant closure .

17 PATIENT COUNSELING INFORMATION

Serious Drug Interactions

Advise patients they should not take Ontralfy if they are taking fluvoxamine or ciprofloxacin because of the increased risk of serious adverse reactions including severe lowering of blood pressure and sedation. Instruct patients to inform their healthcare providers when they start or stop taking any medication because of the risks associated with interaction between Ontralfy and other medicines [see Contraindications (4)and Drug Interactions (7)] .

Ontralfy Dosing and Administration

Tell patients to take Ontralfy exactly as prescribed (consistently either with or without food) [see Dosage and Administration (2.2)] . Inform patients that they should not take more Ontralfy than prescribed because of the risk of adverse events at single doses greater than 8 mg or total daily doses greater than 36 mg. Tell patients that they should not suddenly discontinue Ontralfy, because rebound hypertension and tachycardia may occur [see Warnings and Precautions (5.6)].

Hypotension

Warn patients that they may experience hypotension and to be careful when changing from a lying or sitting to a standing position [see Warnings and Precautions (5.1)].

Sedation

Tell patients that Ontralfy may cause them to become sedated or somnolent and they should be careful when performing activities that require alertness, such as driving a vehicle or operating machinery [see Warnings and Precautions (5.3)]. Tell patients that the sedation may be additive when Ontralfy is taken in conjunction with drugs (baclofen, benzodiazepines) or substances (e.g., alcohol) that act as CNS depressants.

Remind patients that if they depend on their spasticity to sustain posture and balance in locomotion, or whenever spasticity is utilized to obtain increased function, that Ontralfy decreases spasticity and caution should be used.

Hypersensitivity Reactions

Inform patients of the signs and symptoms of severe allergic reactions and instruct them to discontinue Ontralfy and seek immediate medical care should these signs and symptoms occur [see Warnings and Precautions (5.5)].

Manufactured for: Rosemont Pharmaceuticals, LLC, Greenville, SC 29615

ONTRALFY is a trademark of Fidelity Biopharma Co., used under license.

www.rosemontpharmaceuticals.com

SP-PC-048 v.00

Revised 10/2025

PRINCIPAL DISPLAY PANEL - 473 mL Bottle Label

NDC 69528-310-16

Ontralfy™
(tizanidine oral solution)
2 mg/5 mL

16 fl. oz. (473 mL)
Rx only